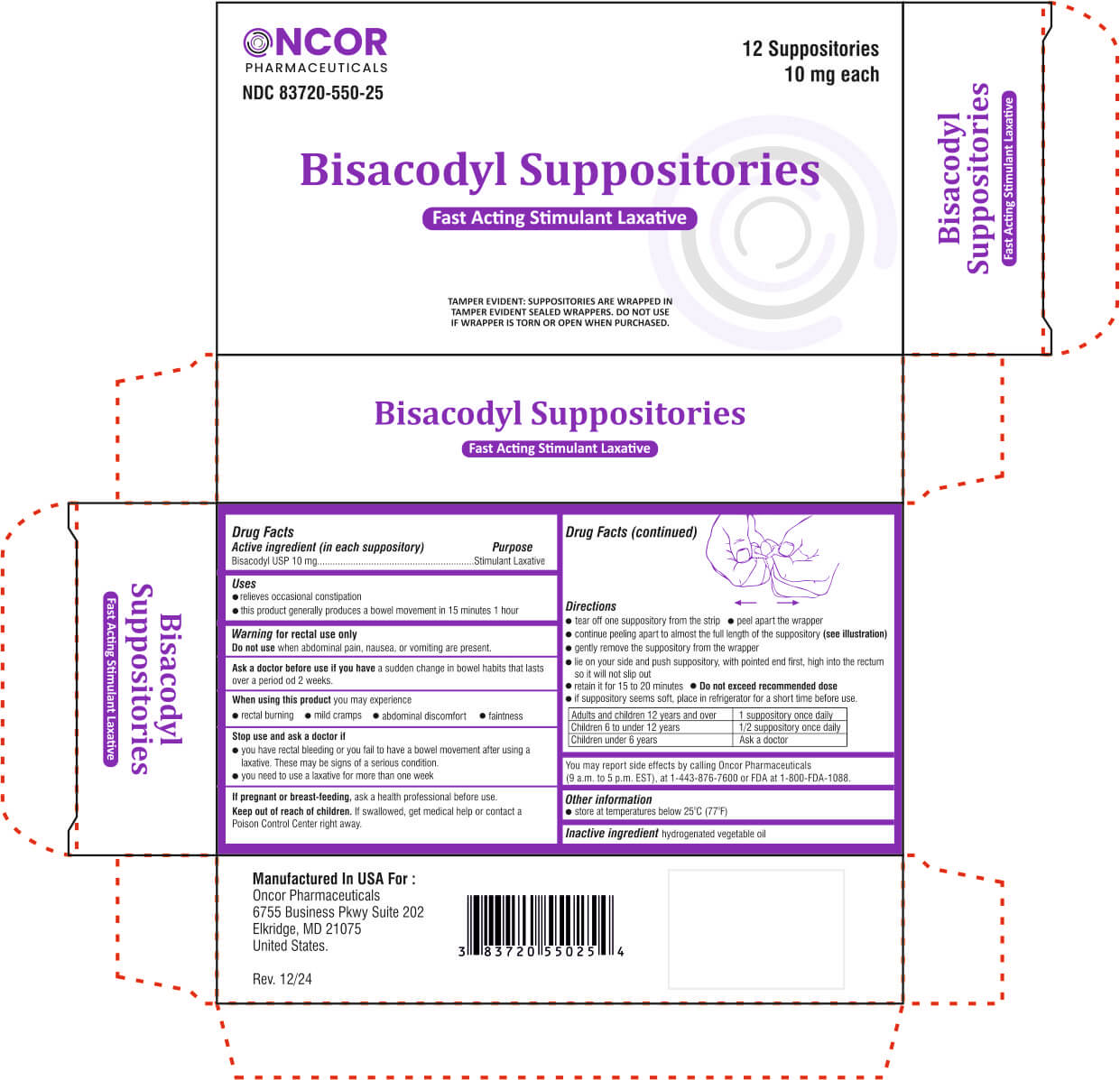 DRUG LABEL: Bisacodyl
NDC: 83720-550 | Form: SUPPOSITORY
Manufacturer: Oncor Pharmaceuticals
Category: otc | Type: HUMAN OTC DRUG LABEL
Date: 20250124

ACTIVE INGREDIENTS: BISACODYL 10 mg/1 1
INACTIVE INGREDIENTS: PALM KERNEL OIL

Bisacodyl Suppositories

Active ingredient (in each suppository) Purpose
Bisacodyl USP 10 mg.............................................................Stimulant Laxative

Uses

- relieves occasional constipation
- this product generally produces a bowel movement in 15 minutes 1 hour

Warning

for rectal use only

Do not usewhen abdominal pain, nausea, or vomiting are present.

Ask a doctor before use if you havea sudden change in bowel habits that lasts over a period od 2 weeks.

When using this productyou may experience

- rectal burning

- mild cramps

- abdominal discomfort

- faintness

Stop use and ask a doctor if

- you have rectal bleeding or you fail to have a bowel movement after using a laxative. These may be signs of a serious condition.

- you need to use a laxative for more than one week

PREGNANCY

If pregnant or breast-feeding,ask a health professional before use.

Keep out of reach of children.

MEDICATION GUIDE

If swallowed, get medical help or contact a Poison Control Center right away.

You may report side effects by calling Oncor Pharmaceuticals
(9 a.m. to 5 p.m. EST), at 1-443-876-7600 or FDA at 1-800-FDA-1088.

Directions

- tear off one suppository from the strip

- peel apart the wrapper

- continue peeling apart to almost the full length of the suppository

- gently remove the suppository from the wrapper

- lie on your side and push suppository, with pointed end first, high into the rectum so it will not slip out

- retain it for 15 to 20 minutes

- Do not exceed recommended dose

- if suppository seems soft, place in refrigerator for a short time before use.

Adults and children 12 years and over | 1 suppository once daily
Children 6 to under 12 years | 1/2 suppository once daily
Children under 6 years | Ask a doctor

Other information

store at temperatures below 25oC (77oF)

Inactive ingredient

hydrogenated vegetable oil

PURPOSE

TAMPER EVIDENT:SUPPOSITORIES ARE WRAPPED IN TAMPER EVIDENT SEALED WRAPPERS. DO NOT USE IF WRAPPER IS TORN OR OPEN WHEN PURCHASED.

PRINCIPAL DISPLAY PANEL

Oncor Pharmaceuticals

NDC 83720-550-25

12 Suppositories

10 mg each

Bisacodyl Suppositories

Fast Acting Smulant Laxative

Manufactured In USA For :

Oncor Pharmaceuticals
6755 Business Pkwy Suite 202
Elkridge, MD 21075
United States.

Rev. 12/24